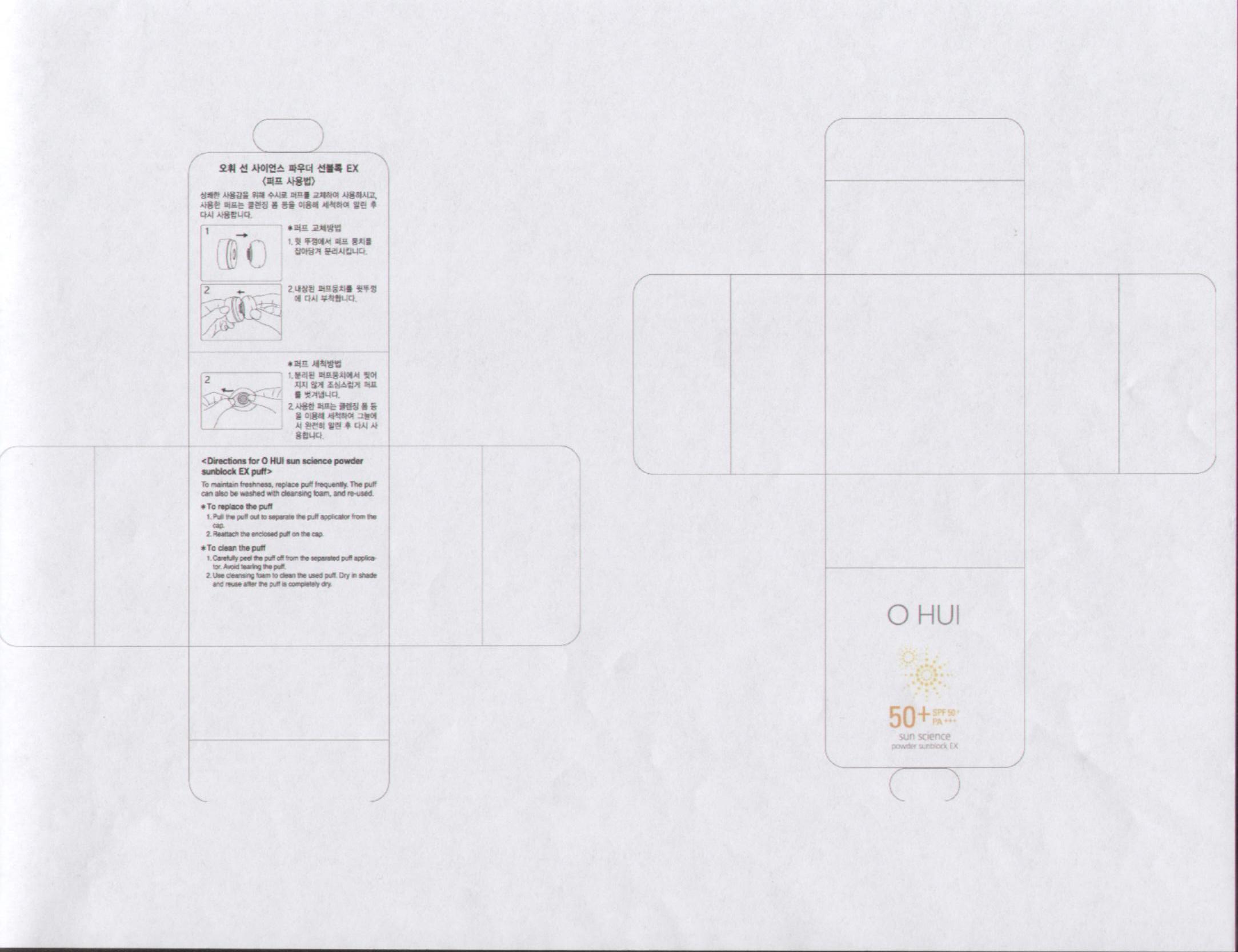 DRUG LABEL: OHUI Sun Science Powder Sun Block Natural Skin
NDC: 53208-437 | Form: POWDER
Manufacturer: LG Household and Healthcare, Inc.
Category: otc | Type: HUMAN OTC DRUG LABEL
Date: 20100504

ACTIVE INGREDIENTS: OCTINOXATE 7 g/100 g; Zinc Oxide 5 g/100 g; Titanium Dioxide 2.5 g/100 g; BISOCTRIZOLE 2 g/100 g
INACTIVE INGREDIENTS: Talc; SILICON DIOXIDE; Aluminum Hydroxide; Dimethicone; Methylparaben; PropylParaben; Stearic Acid; FERRIC OXIDE YELLOW

Drug Facts

ACTIVE INGREDIENT

OCTINOXATE 7g/100g

Zinc Oxide 5g/100g

Titanium Dioxide 2.5g/100g

BISOCTRIZOLE 2g/100g

WARNINGS AND PRECAUTIONS

For external use only

Keep out of reach of children. Is swallowed, get medical help or contact a Poison Control Center right away.

WHEN USING

Keep out of eyes. Rinse with water to remove.

Stop use if a rash or irritation develops and lasts.

PACKAGE LABEL

Ohui

50+

SPF 50+ PA +++

sun science

powder sunblock EX